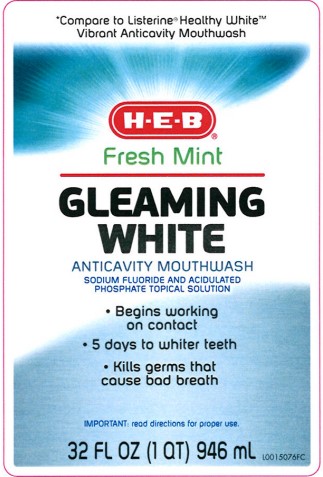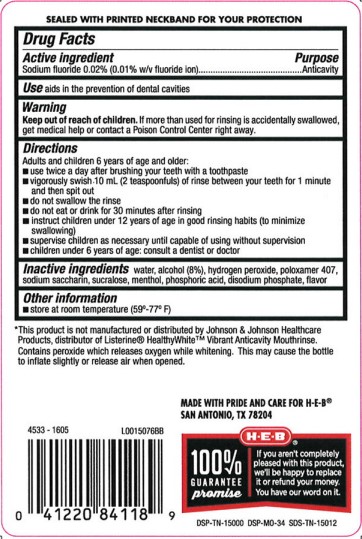 DRUG LABEL: Anticavity
NDC: 37808-435 | Form: MOUTHWASH
Manufacturer: H E B
Category: otc | Type: HUMAN OTC DRUG LABEL
Date: 20260224

ACTIVE INGREDIENTS: SODIUM FLUORIDE 0.1 mg/1 mL
INACTIVE INGREDIENTS: WATER; ALCOHOL; HYDROGEN PEROXIDE; POLOXAMER 407; SACCHARIN SODIUM; SUCRALOSE; MENTHOL; PHOSPHORIC ACID; SODIUM PHOSPHATE, DIBASIC, ANHYDROUS

HEB 435.000/435AA
Glowing White Anticavity Mouthrinse

Tamper Evident Statement

SEALED WITH PRINTED NECKBAND FOR YOUR PROTECTION

Active Ingredient

Sodium fluoride 0.02% (0.01% w/v fluoride ion)

Purpose

Anticavity

Use

Aids in the prevention of dental cavities

Warnings

For this product

Keep out of reach of children.

If more than used for rinsing is accidentally swallowed, get medical help or contact a Poison Control Center right away.

Directions

Adults and children 6 years of age and older:

- use twice a day after brushing your teeth with a toothpaste
- vigorously swish 10 mL (2 teaspoonfuls) of rinse between your teeth for 1 minute and then spit out
- do not swallow the rinse
- do not eat or drink for 30 minutes after rinsing
- instruct children under 12 years of age in good rinsing habits (to minimize swallowing)
- supervise children as necessary until capable of using without supervision
- children under 6 years of age: consult a dentist or doctor

Inactive ingredients

water, alcohol (8%), hydrogen peroxide, poloxamer 407, sodium saccharin, sucralose, menthol, phosphoric acid, disodium phosphate, flavor

Other information

store at room temperature (59º-77ºF)

Disclaimer

*This product is not manufactured or distributed by Johnson & Johnson Healthcare Products, distributor of Listerine®HealthyWhite®Vibrant Anticavity Mouthrinse.

other information

Contains peroxide which releases oxgen while whitening. This may cause the bottle to inflate slightly or release air when opened.

Adverse reactions section

MADE WITH PRIDE AND CARE FOR H-E-B®

SAN ANTONIO, TX 78204

HEB 100& GUARANTEE promise

If you aren't completely pleased with this product, we'll be happy to replace it or refund your money. You have our word on it.

DSP-TN-15000

DSP-MO-34

SDS-TN-15012

principal display panel

*Compare to Listerine®Healthy White™ Vibrant Anticavity Mouthwash

H-E-B®

Fresh Mint

GLEAMING

WHITE

ANTICAVITY MOUTHRINSE

SODIUM FLUORIDE AND ACIDULATED

PHOSPHATE TOPICAL SOLUTION

- Begins working on contact
- 5 days to whiter teeth
- Kills germs that cause bad breath

IMPORTANT: read directions for proper use.

32 FL OZ (1 QT) 946 mL